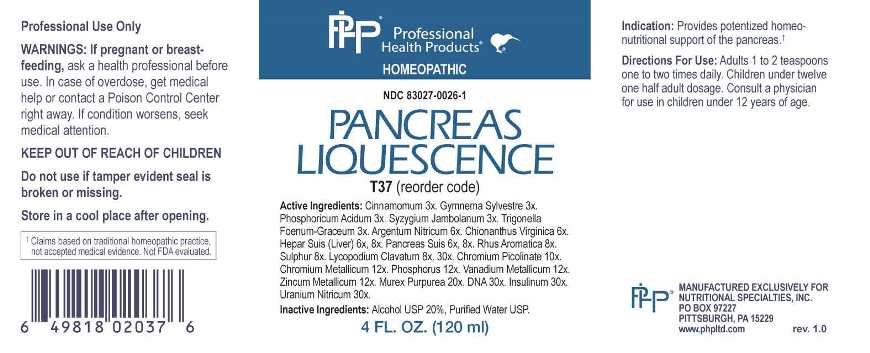 DRUG LABEL: Pancreas Liquescence
NDC: 83027-0026 | Form: LIQUID
Manufacturer: Nutritional Specialties, Inc.
Category: homeopathic | Type: HUMAN OTC DRUG LABEL
Date: 20230327

ACTIVE INGREDIENTS: CINNAMON 3 [hp_X]/1 mL; GYMNEMA SYLVESTRE LEAF 3 [hp_X]/1 mL; PHOSPHORIC ACID 3 [hp_X]/1 mL; SYZYGIUM CUMINI SEED 3 [hp_X]/1 mL; FENUGREEK SEED 3 [hp_X]/1 mL; SILVER NITRATE 6 [hp_X]/1 mL; CHIONANTHUS VIRGINICUS ROOT BARK 6 [hp_X]/1 mL; PORK LIVER 6 [hp_X]/1 mL; SUS SCROFA PANCREAS 6 [hp_X]/1 mL; RHUS AROMATICA ROOT BARK 8 [hp_X]/1 mL; SULFUR 8 [hp_X]/1 mL; LYCOPODIUM CLAVATUM SPORE 8 [hp_X]/1 mL; CHROMIUM PICOLINATE 10 [hp_X]/1 mL; CHROMIUM 12 [hp_X]/1 mL; PHOSPHORUS 12 [hp_X]/1 mL; VANADIUM 12 [hp_X]/1 mL; ZINC 12 [hp_X]/1 mL; HEXAPLEX TRUNCULUS HYPOBRANCHIAL GLAND JUICE 20 [hp_X]/1 mL; HERRING SPERM DNA 30 [hp_X]/1 mL; INSULIN HUMAN 30 [hp_X]/1 mL; URANYL NITRATE HEXAHYDRATE 30 [hp_X]/1 mL
INACTIVE INGREDIENTS: WATER; ALCOHOL

DRUG FACTS:

ACTIVE INGREDIENTS:

Cinnamomum 3X, Gymnema Sylvestre 3X, Phosphoricum Acidum 3X, Syzygium Jambolanum 3X, Trigonella Foenum-Graceum 3X, Argentum Nitricum 6X, Chionanthus Virginica 6X, Hepar Suis (Liver) 6X, 8X, Pancreas Suis 6X, 8X, Rhus Aromatica 8X, Sulphur 8X, Lycopodium Clavatum 8X, 30X, Chromium Picolinate 10X, Chromium Metallicum 12X, Phosphorus 12X, Vanadium Metallicum 12X, Zincum Metallicum 12X, Murex Purpurea 20X, DNA 30X, Insulinum 30X, Uranium Nitricum 30X.

PURPOSE:

Provides potentized homeo-nutritional support of the pancreas.†

†Claims based on traditional homeopathic practice, not accepted medical evidence. Not FDA evaluated.

WARNINGS:

Professional Use Only

If pregnant or breast-feeding, ask a health professional before use.

In case of overdose, get medical help or contact a Poison Control Center right away.

If condition worsens, seek medical attention.

KEEP OUT OF REACH OF CHILDREN

Do not use if tamper evident seal is broken or missing.

Store in a cool place after opening

KEEP OUT OF REACH OF CHILDREN:

In case of overdose, get medical help or contact a Poison Control Center right away.

DIRECTIONS:

Adults 1 to 2 teaspoons one to two times daily. Children under twelve one half adult dosage. Consult a physician for use in children under 12 years of age.

INDICATIONS:

Provides potentized homeo-nutritional support of the pancreas.†

†Claims based on traditional homeopathic practice, not accepted medical evidence. Not FDA evaluated.

INACTIVE INGREDIENTS:

Alcohol USP 20%, Purified Water USP.

QUESTIONS:

MANUFACTURED EXCLUSIVELY FOR

NUTRITIONAL SPECIALTIES, INC.

PO BOX 97227

PITTSBURG, PA 15229

www.phpltd.com

PACKAGE LABEL DISPLAY:

Professional

Health Products

HOMEOPATHIC

NDC 83027-0026-1

PANCREAS

LIQUESCENCE

4 FL. OZ (120 ml)